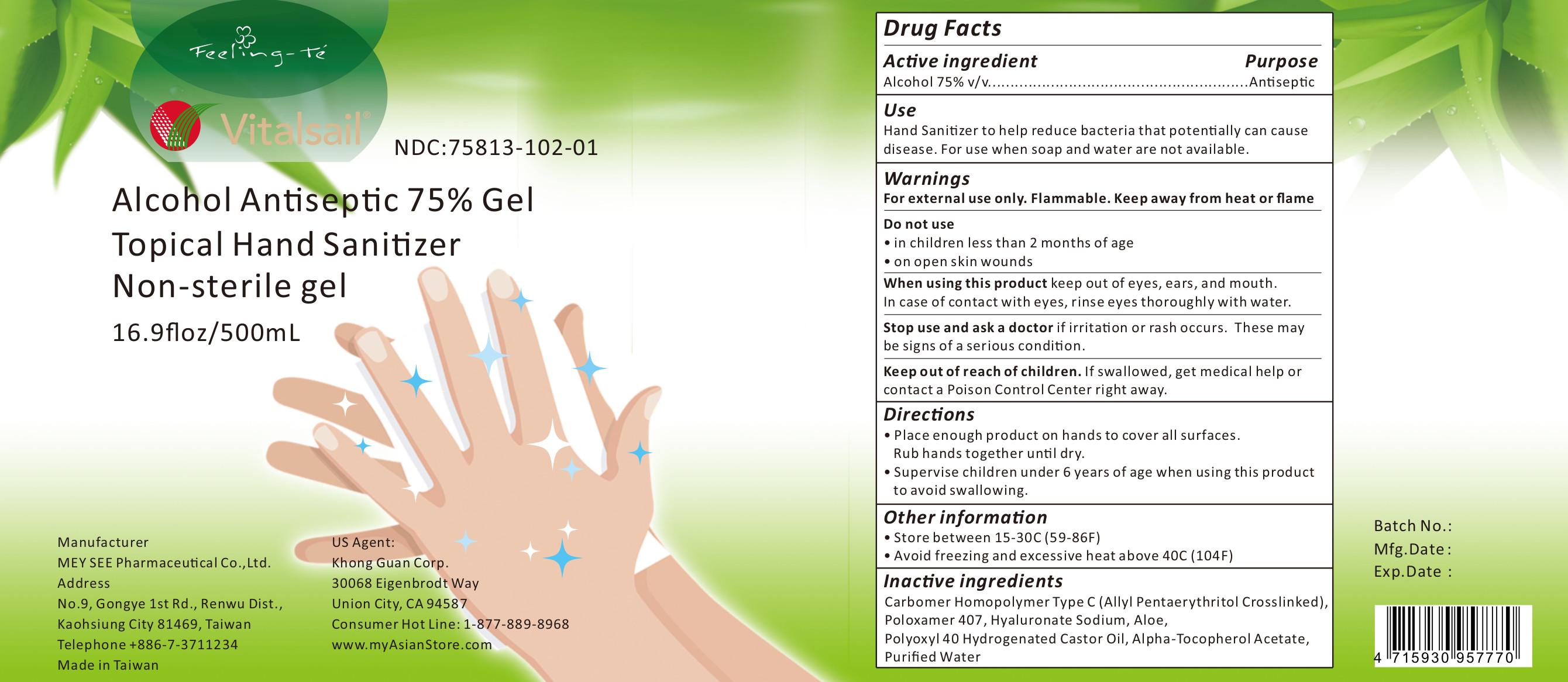 DRUG LABEL: Vitalsail
NDC: 75813-102 | Form: GEL
Manufacturer: MEY SEE PHARMACEUTICAL CO., LTD.
Category: otc | Type: HUMAN OTC DRUG LABEL
Date: 20200622

ACTIVE INGREDIENTS: ALCOHOL 75 mL/100 mL
INACTIVE INGREDIENTS: Carbomer Homopolymer Type C (Allyl Pentaerythritol Crosslinked); poloxamer 407; hyaluronate sodium; aloe; polyoxyl 40 hydrogenated castor oil; Alpha-Tocopherol Acetate; water

Vitalsail Alcohol Antiseptic 75% Gel

Active Ingredient(s)

Alcohol 75% v/v. Purpose: Antiseptic

Purpose

Antiseptic, Hand Sanitizer

Use

Hand Sanitizer to help reduce bacteria that potentially can cause disease. For use when soap and water are not available.

Warnings

For external use only. Flammable. Keep away from heat or flame

Do not use

- in children less than 2 months of age
- on open skin wounds

When using this product keep out of eyes, ears, and mouth. In case of contact with eyes, rinse eyes thoroughly with water.

Stop use and ask a doctor if irritation or rash occurs. These may be signs of a serious condition.

Keep out of reach of children. If swallowed, get medical help or contact a Poison Control Center right away.

Directions

- Place enough product on hands to cover all surfaces. Rub hands together until dry.
- Supervise children under 6 years of age when using this product to avoid swallowing.

Other information

- Store between 15-30C (59-86F)
- Avoid freezing and excessive heat above 40C (104F)

Inactive ingredients

Carbomer Homopolymer Type C (Allyl Pentaerythritol Crosslinked), Poloxamer 407, Sodium Hyaluronate,
Aloe, Polyoxyl 40 Hydrogenated Castor Oil, Alpha-Tocopherol Acetate, Purified Water

Label

500ml NDC:75813-102-01